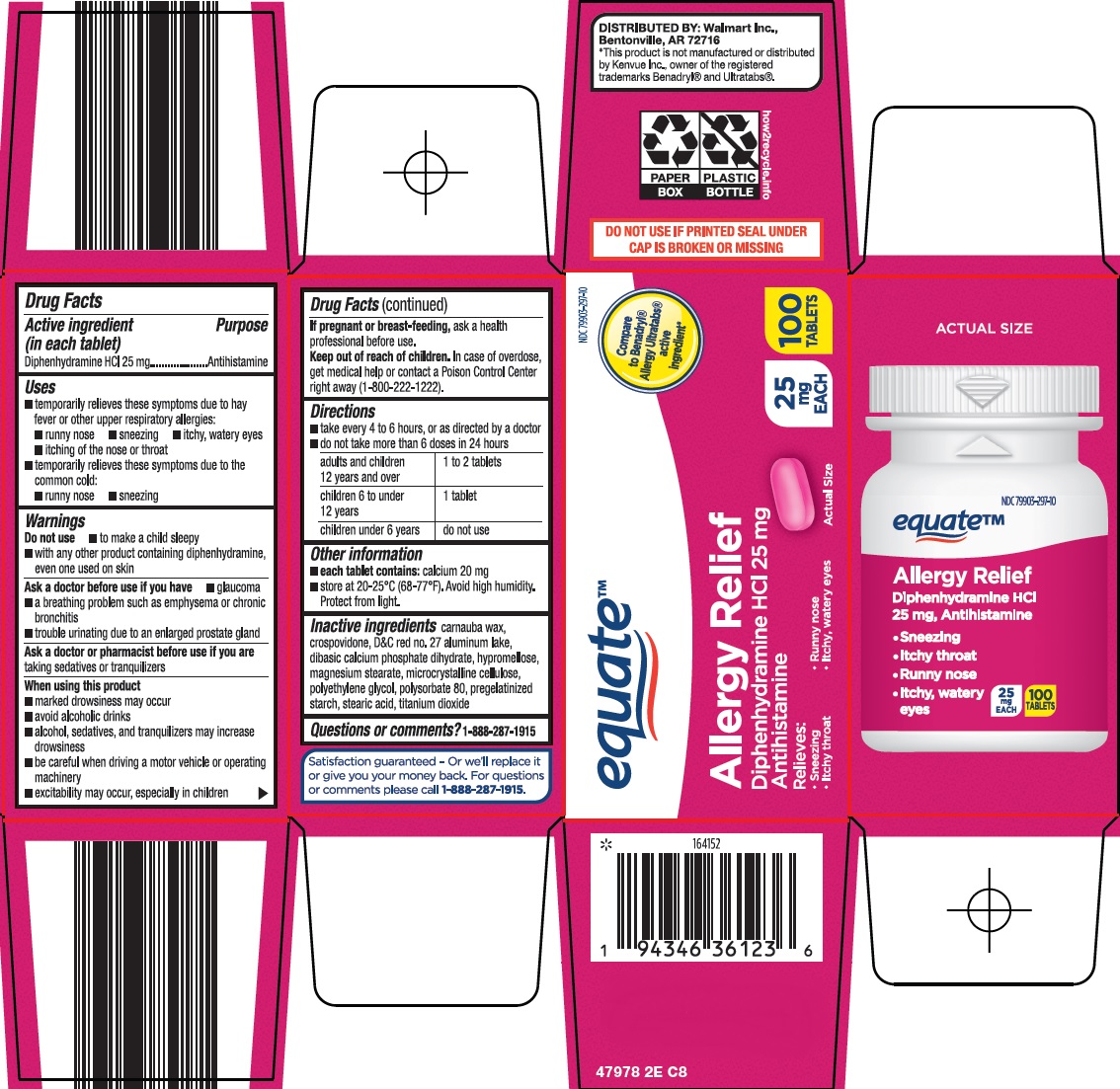 DRUG LABEL: equate allergy relief
NDC: 79903-297 | Form: TABLET
Manufacturer: WALMART INC.
Category: otc | Type: HUMAN OTC DRUG LABEL
Date: 20250815

ACTIVE INGREDIENTS: DIPHENHYDRAMINE HYDROCHLORIDE 25 mg/1 1
INACTIVE INGREDIENTS: CARNAUBA WAX; CROSPOVIDONE, UNSPECIFIED; D&C RED NO. 27 ALUMINUM LAKE; DIBASIC CALCIUM PHOSPHATE DIHYDRATE; HYPROMELLOSE, UNSPECIFIED; MAGNESIUM STEARATE; MICROCRYSTALLINE CELLULOSE; POLYETHYLENE GLYCOL, UNSPECIFIED; POLYSORBATE 80; STEARIC ACID; TITANIUM DIOXIDE

Wal-Mart Allergy Relief Drug Facts

Active ingredient (in each tablet)

Diphenhydramine HCl 25 mg

Purpose

Antihistamine

Uses

- temporarily relieves these symptoms due to hay fever or other upper respiratory allergies:
- runny nose
- sneezing
- itchy, watery eyes
- itching of the nose or throat
- temporarily relieves these symptoms of the common cold:
- runny nose
- sneezing

Warnings

Do not use

- with any other product containing diphenhydramine, even one used on skin
- to make a child sleepy

Ask a doctor before use if you have

- glaucoma
- trouble urinating due to an enlarged prostate gland
- a breathing problem such as emphysema or chronic bronchitis

Ask a doctor or pharmacist before use if you are

taking sedatives or tranquilizers

When using this product

- marked drowsiness may occur
- avoid alcoholic drinks
- alcohol, sedatives, and tranquilizers may increase drowsiness
- be careful when driving a motor vehicle or operating machinery
- excitability may occur, especially in children

If pregnant or breast-feeding,

ask a health professional before use.

Keep out of reach of children.

In case of overdose, get medical help or contact a Poison Control Center right away (1-800-222-1222).

Directions

- take every 4 to 6 hours, or as directed by a doctor
- do not take more than 6 doses in 24 hours

adults and children 12 years and over | 1 to 2 tablets
children 6 to under 12 years | 1 tablet
children under 6 years | do not use

Other information

- each tablet contains: calcium 20 mg
- store at 20-25°C (68-77°F). Avoid high humidity. Protect from light.

Inactive ingredients

carnauba wax, crospovidone, D&C red no. 27 aluminum lake, dibasic calcium phosphate dihydrate, hypromellose, magnesium stearate, microcrystalline cellulose, polyethylene glycol, polysorbate 80, pregelatinized starch, stearic acid, titanium dioxide

Questions or comments?

1-888-287-1915

Principal Display Panel

equate™

Compare to Benadryl® Allergy Ultratabs® active ingredient

Allergy Relief

Diphenhydramine HCl 25 mg

Antihistamine

Relieves:

• Sneezing

• Runny nose

• Itchy throat

• Itchy, watery eyes

Actual Size

25 mg EACH

100 TABLETS